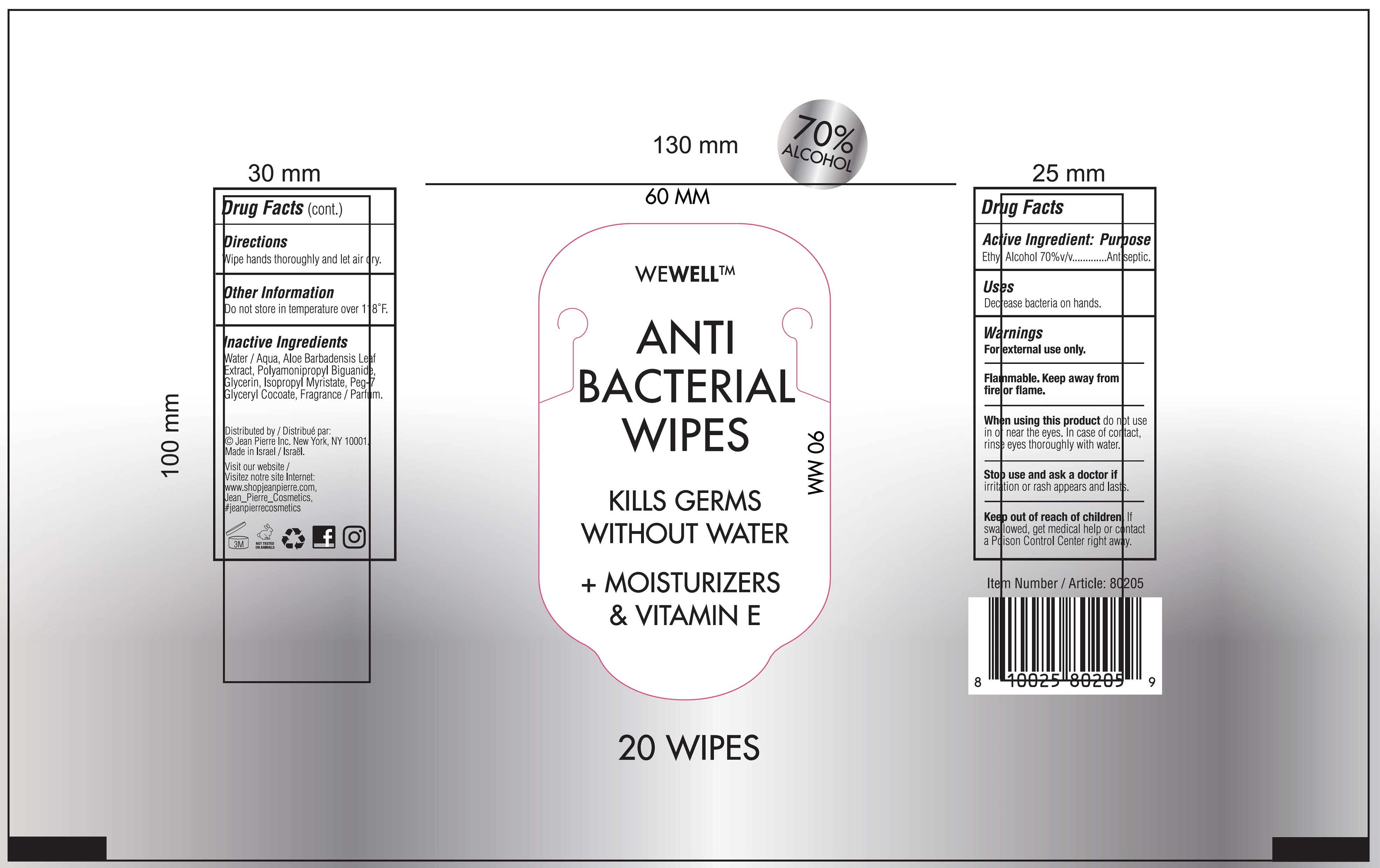 DRUG LABEL: WeWell Anti Bacterial Wipes
NDC: 70483-019 | Form: CLOTH
Manufacturer: Jean Pierre Inc.
Category: otc | Type: HUMAN OTC DRUG LABEL
Date: 20201028

ACTIVE INGREDIENTS: ALCOHOL 0.7 mL/1 mL
INACTIVE INGREDIENTS: WATER; ALOE VERA LEAF; POLYAMINOPROPYL BIGUANIDE; GLYCERIN; ISOPROPYL MYRISTATE; PEG-7 GLYCERYL COCOATE

WeWell Anti Bacterial Wipes

Active Ingredient:

Ethyl Alcohol 70% v/v

Purpose

Antiseptic

Uses

Decrease bacteria on hands.

Warnings

For external use only.

Flammable. Keep away from fire or flame.

When using this product

do not use in or near the eyes. In case of contact, rinse eye thoroughly with water.

Stop use and ask a doctor if

irritation or rash appears and lasts.

Keep out of reach of children.

If swallowed, get medical help or contact a Poison Control Center right away.

Directions

Wipe hands thoroughly and let air dry.

Other Information

Do not store in temperature over 118°F.

Inactive Ingredients

Water / Aqua, Aloe Barbadeni Leaf Extract, Polyamonipropyl Biguanide, Glycerin, Isopropyl Myristate, Peg-7 Glyceryl Cocoate, Fragrance/ Parfum.